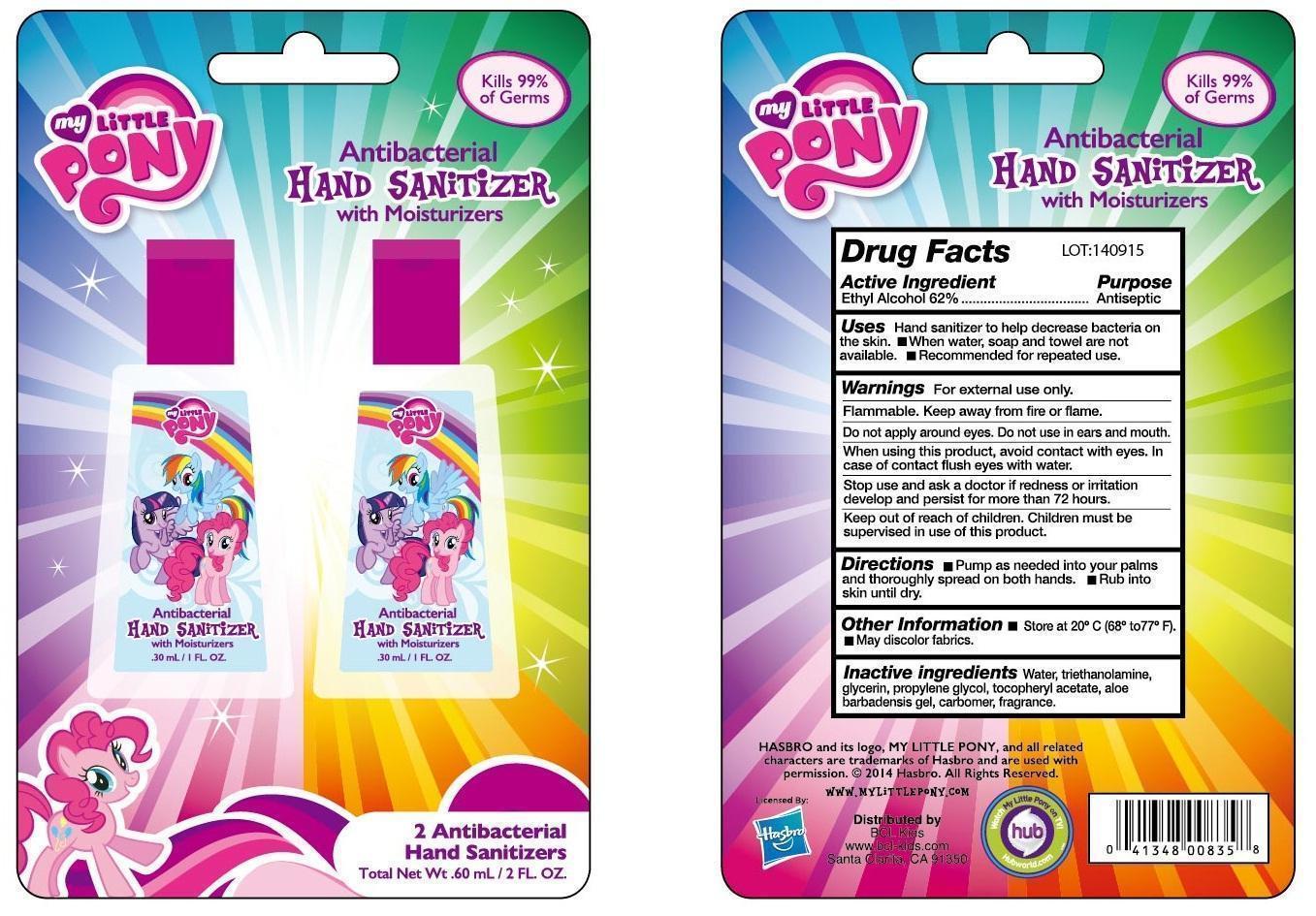 DRUG LABEL: My Little Pony Antibacterial Hand Sanitizer with Moisturizers
NDC: 40104-204 | Form: GEL
Manufacturer: Ningbo Pulisi Daily Chemical Products Co., Ltd.
Category: otc | Type: HUMAN OTC DRUG LABEL
Date: 20150205

ACTIVE INGREDIENTS: ALCOHOL 62 mL/100 mL
INACTIVE INGREDIENTS: CAPRYLYL GLYCOL; GLYCERIN; ISOPROPYL ALCOHOL; ISOPROPYL MYRISTATE; POLYOXYL 40 HYDROGENATED CASTOR OIL; PHENOXYETHANOL; PROPYLENE GLYCOL; ALPHA-TOCOPHEROL ACETATE; TROLAMINE; WATER

Drug Facts

Active ingredient
Ethyl Alcohol 62% v/v

Purpose
Antiseptic

INDICATIONS AND USAGE

Uses • hand sanitizer to help reduce bacteria on the skin, when water, soap and towel are not available. • recommended for repeated use.

WARNINGS

Warnings • Flammable • Keep away from fire or flame • For external use only

When using this product • avoid contact with eyes • in case of eye contact flush eyes with water. • stop use and ask a doctor if redness or irritation develop and persist for more than 72 hours.

Keep out of reach of children. Children must be supervised in use of this product.

Other Information • store at 20°C(68-77°F). • May discolor fabrics.

DOSAGE AND ADMINISTRATION

Directions •Pump as needed into your palm to thoroughly spread on both hands. •rub into the skin until dry.

INACTIVE INGREDIENT

Inactive ingredients caprylyl glycol, carbomer, fragrance, glycerin, isopropyl alcohol, isopropyl myristate, PEG-40 hydrogenated castor oil, phenoxyethanol, propylene glycol, tocopheryl acetate, triethanolamine, water.